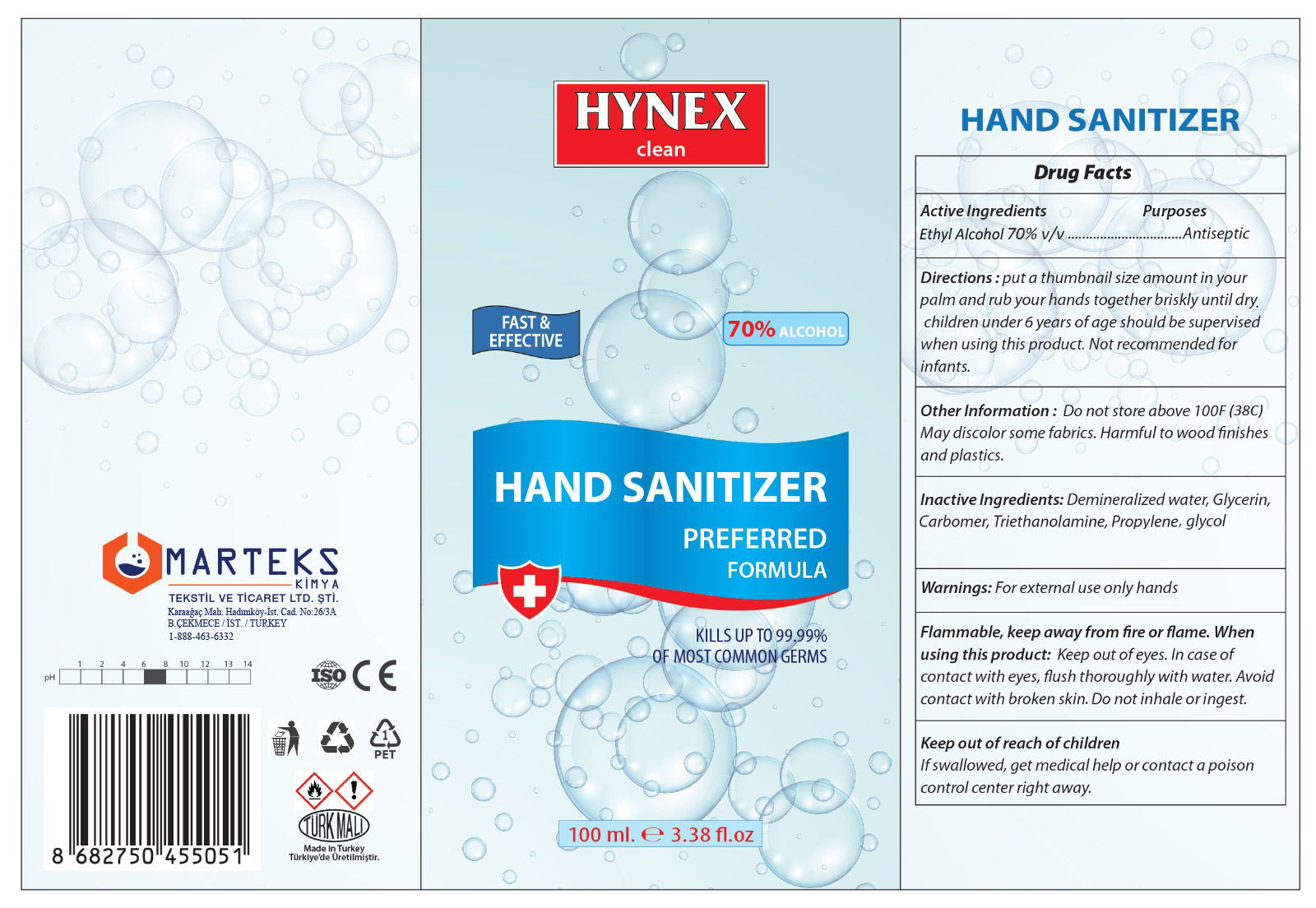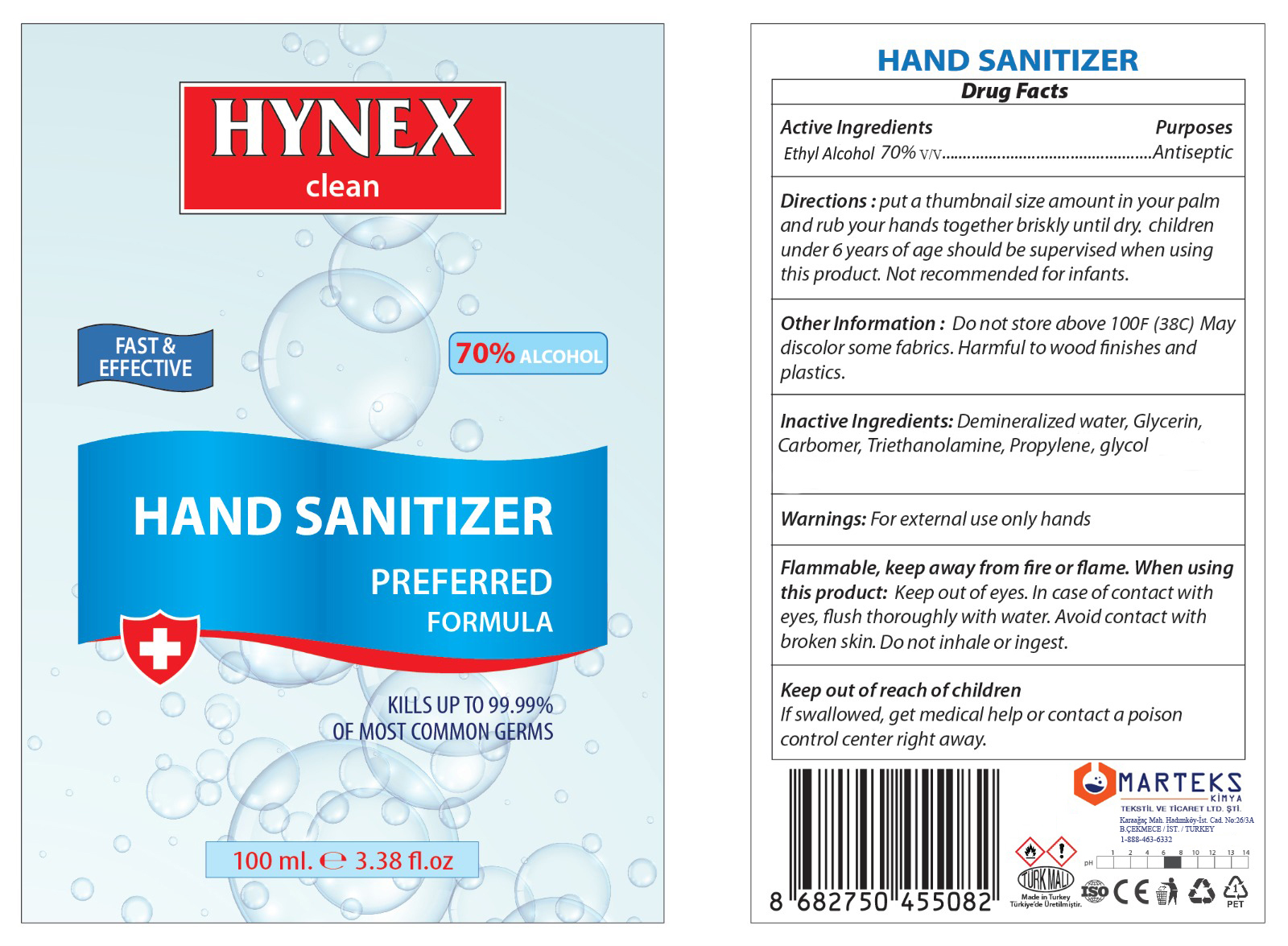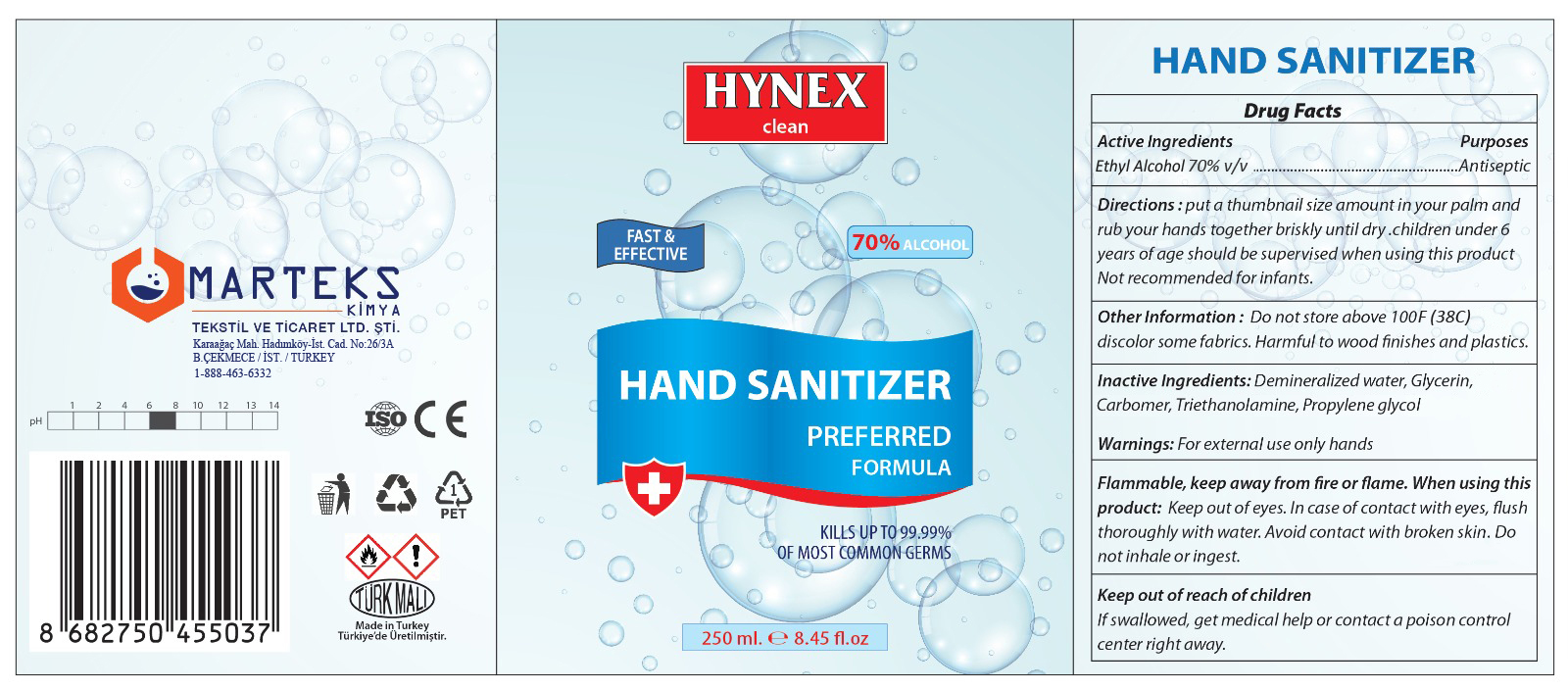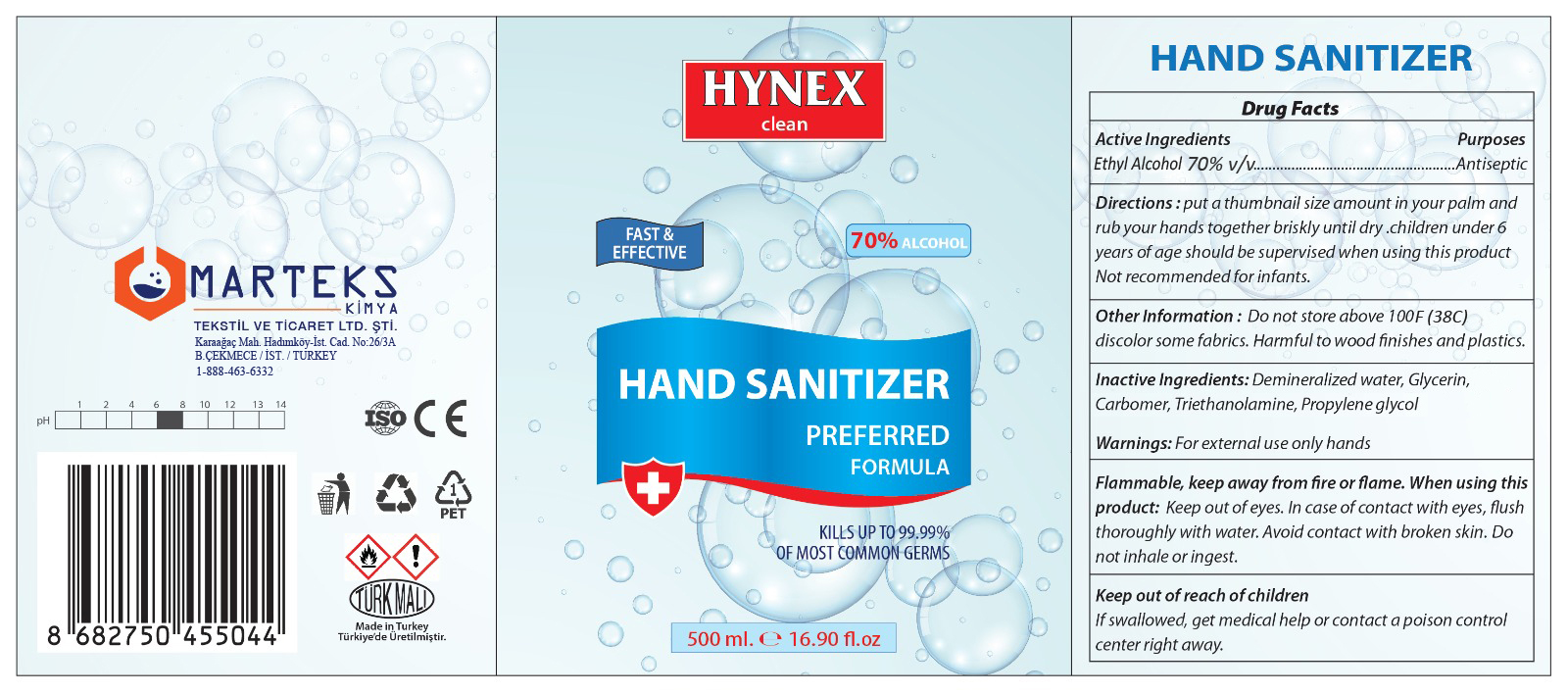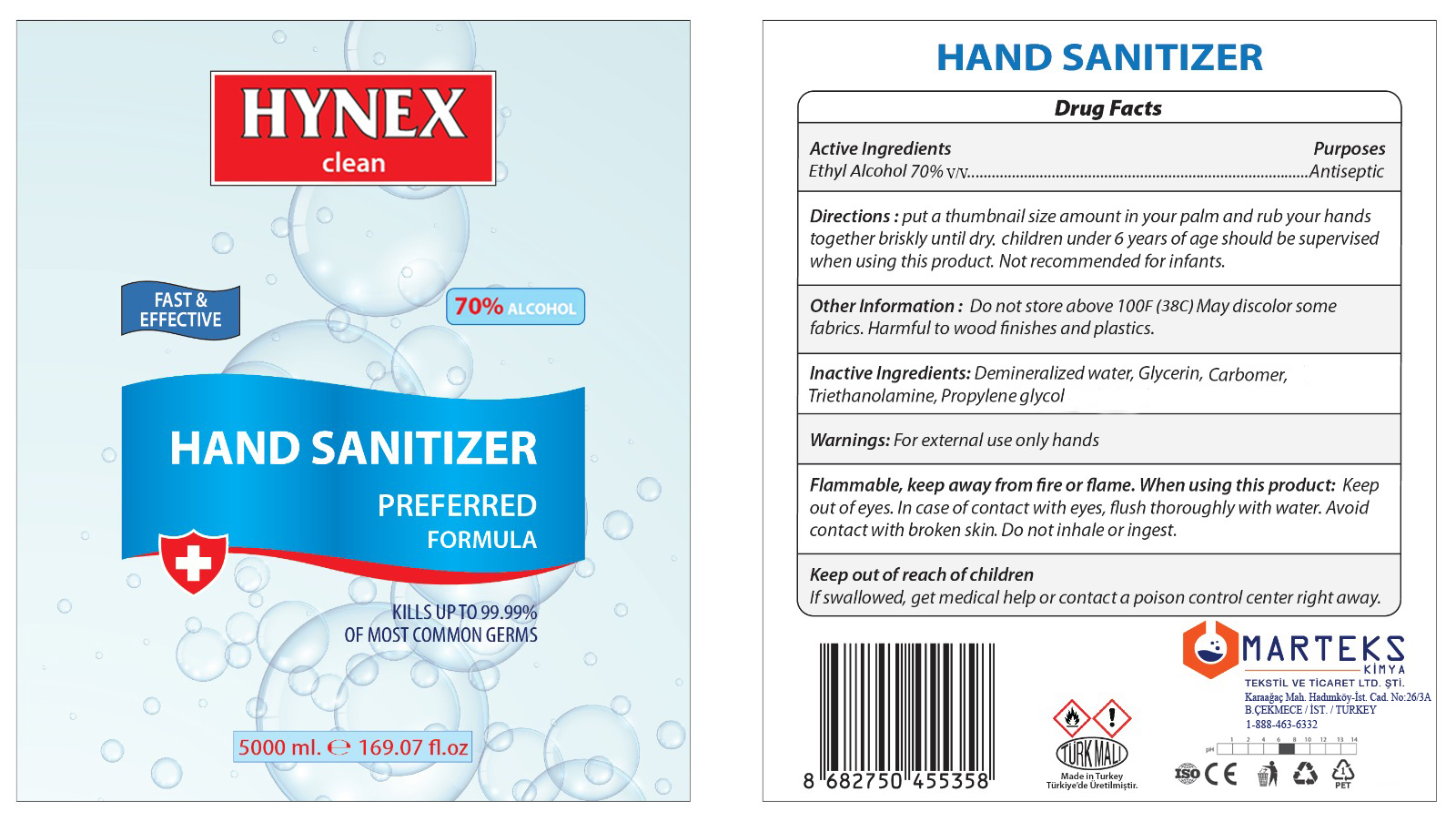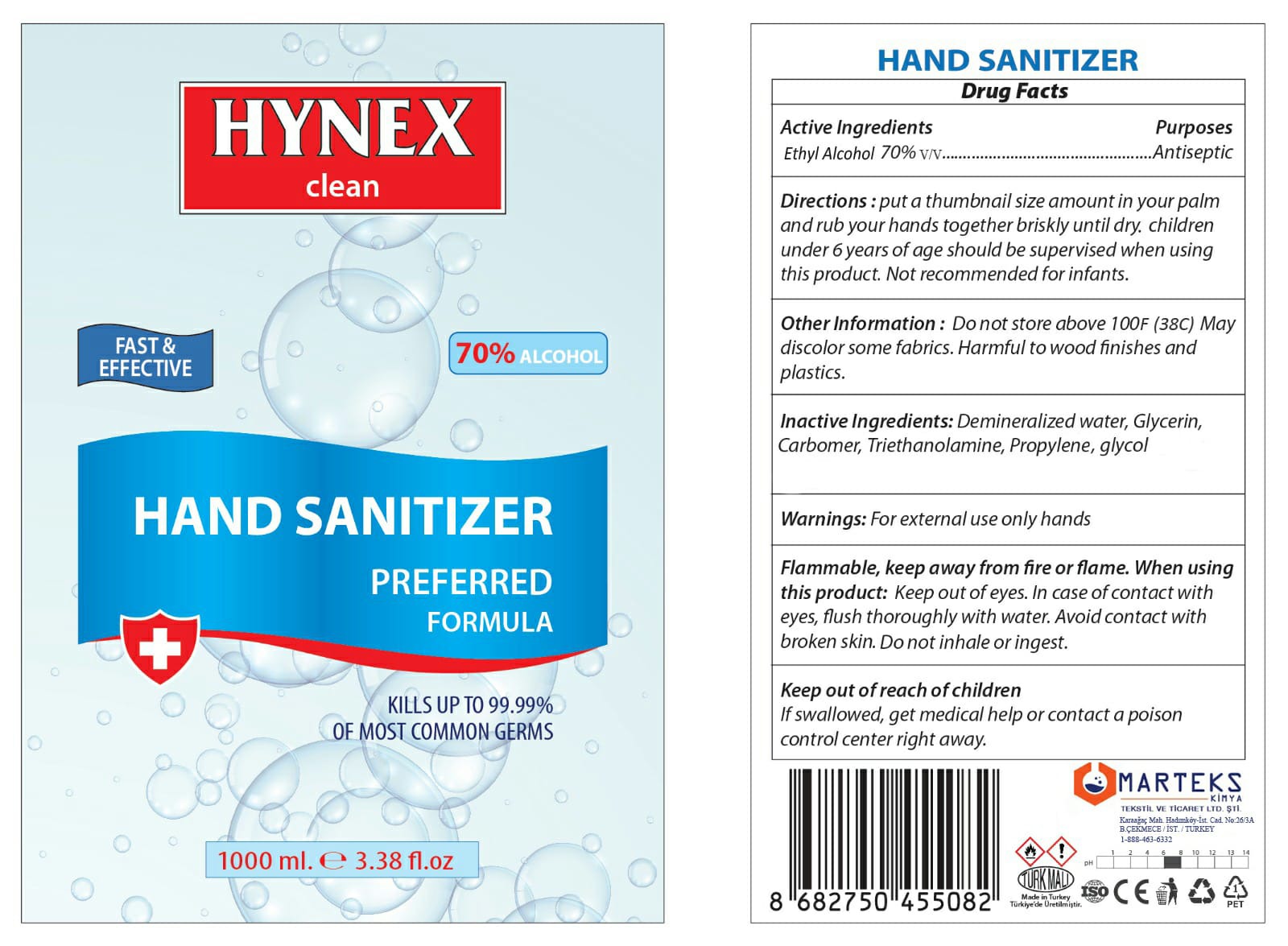 DRUG LABEL: Hynex Clean
NDC: 80565-001 | Form: SOLUTION
Manufacturer: Marteks Kimya Tekstil Ve Ticaret Limited Sirketi
Category: otc | Type: HUMAN OTC DRUG LABEL
Date: 20201002

ACTIVE INGREDIENTS: ALCOHOL 70 mL/100 mL
INACTIVE INGREDIENTS: WATER; GLYCERIN; TROLAMINE; PROPYLENE GLYCOL; CARBOMER 940

Active Ingredient(s)

Ethyl Alcohol 70% v/v.

Purpose

Antiseptic

Directions

put a thumbnail size amount in your palm and rub your hands together briskly until dry.

Directions

children under 6 years of age should be supervised when using this product. Not recommended for infants.

Other information

Do you not store above 100F (38C) May discolor some fabrics. Harmful to wood finishes and plastics.

Inactive ingredients

Demineralized water, Glycerin, Carbomer, Triethanolamine, Propylene glycol

Warnings

For external use only hands

When Using

Flammable, keep away from fire or flame. When using this product: Keep out of eyes. In case of contact with eyes, flush thoroughly with water. Avoid contact with broken skin. Do not inhale or ingest.

KEEP OUT OF REACH OF CHILDREN

If swallowed, get medical help or contact a poison control center right away.

Package Label - Principal Display Panel

100 mL NDC: 80565-001-01

100 mL NDC: 80565-001-11

250 mL NDC: 80565-001-25

500 mL NDC: 80565-001-05

5000 mL NDC: 80565-001-50

1000 mL NDC: 80565-001-10